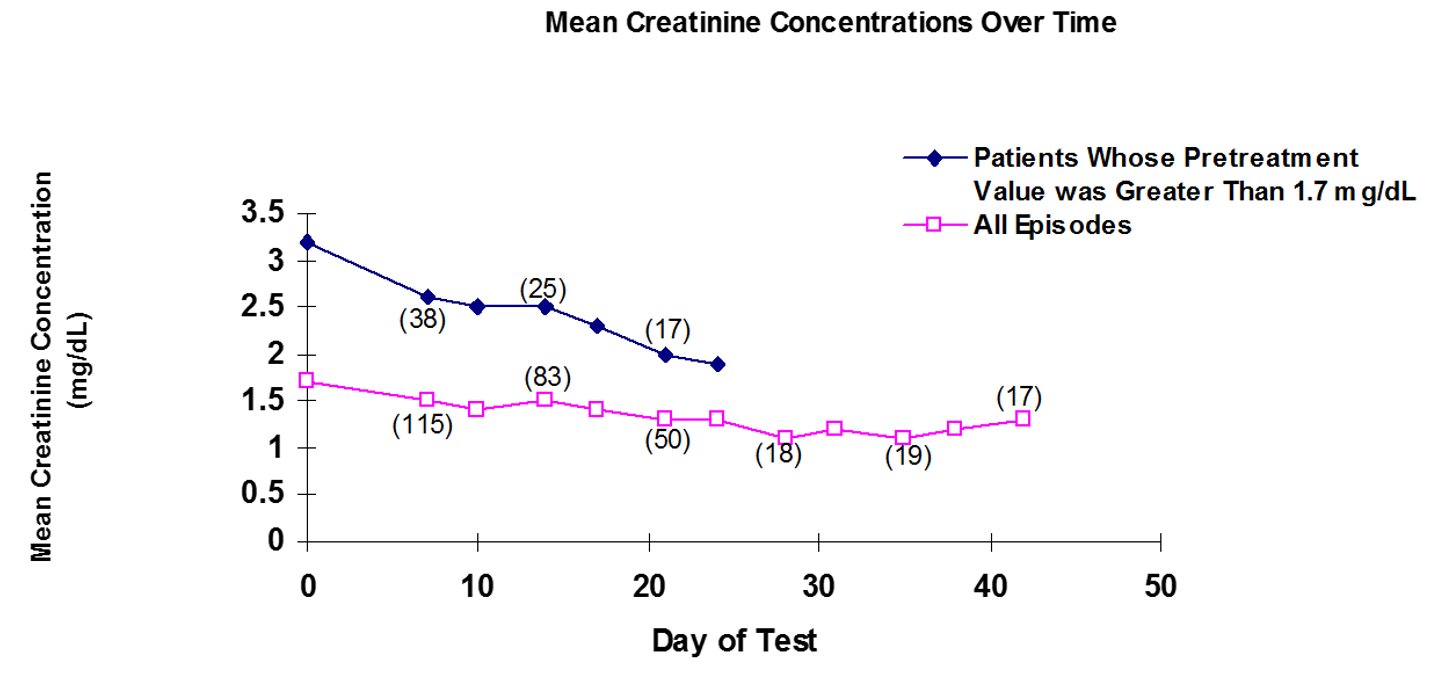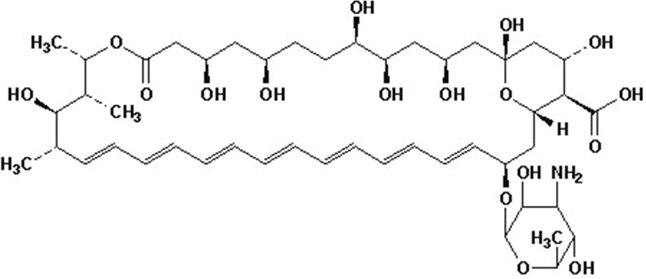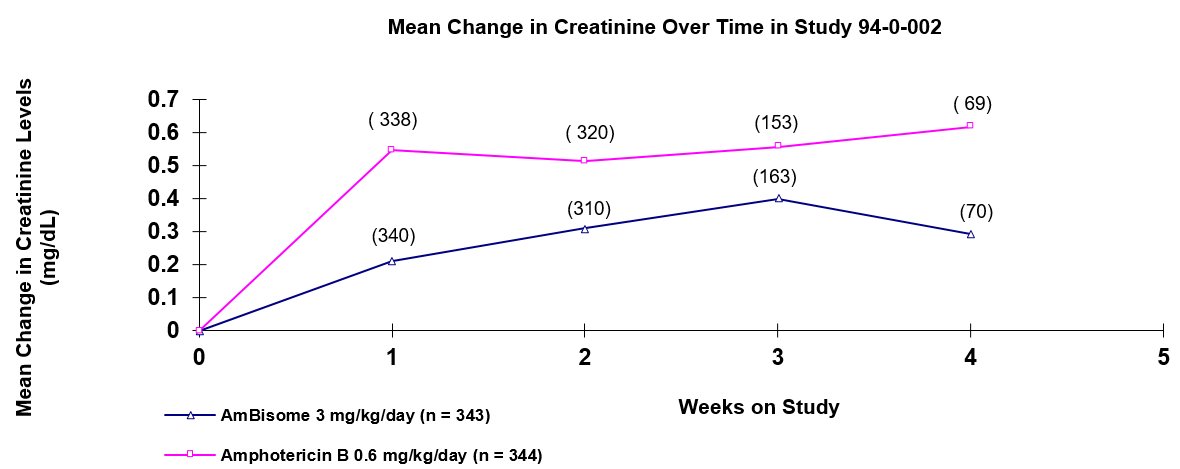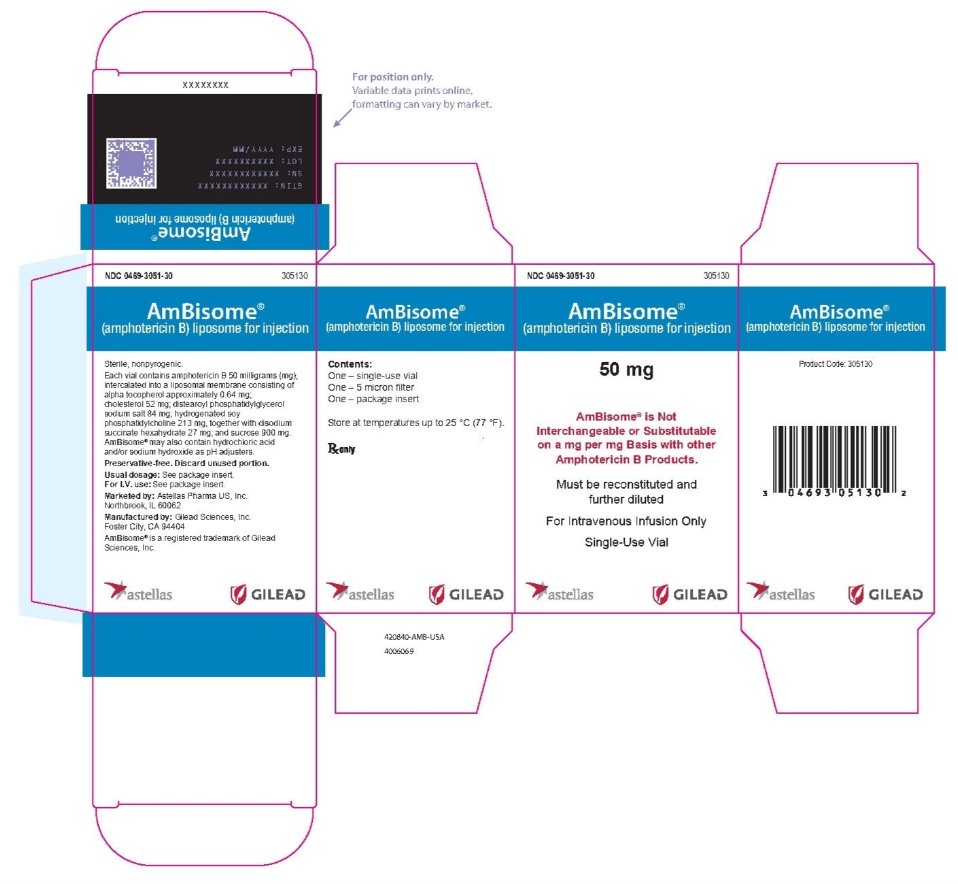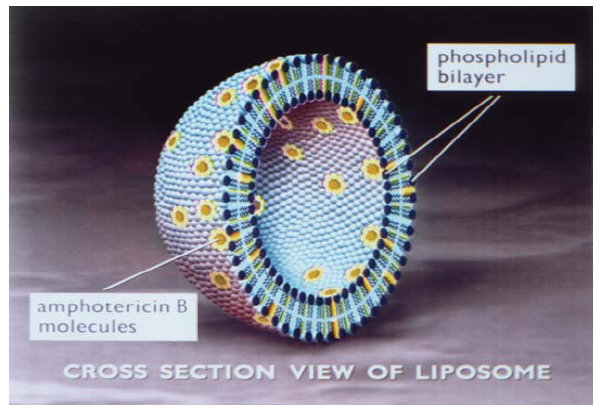 DRUG LABEL: AmBisome
NDC: 0469-3051 | Form: INJECTION, POWDER, LYOPHILIZED, FOR SOLUTION
Manufacturer: Astellas Pharma US, Inc.
Category: prescription | Type: HUMAN PRESCRIPTION DRUG LABEL
Date: 20250611

ACTIVE INGREDIENTS: AMPHOTERICIN B 50 mg/12.5 mL
INACTIVE INGREDIENTS: .ALPHA.-TOCOPHEROL; CHOLESTEROL; SODIUM SUCCINATE HEXAHYDRATE; DISTEAROYLPHOSPHATIDYLGLYCEROL, DL-; HYDROGENATED SOYBEAN LECITHIN; WATER; SUCROSE

AmBisome®
(amphotericin B) liposome for injection

DESCRIPTION

AmBisome® for Injection is a sterile, non-pyrogenic lyophilized product for intravenous infusion. Each vial contains amphotericin B 50 milligrams (mg), intercalated into a liposomal membrane consisting of alpha tocopherol approximately 0.64 mg; cholesterol 52 mg; distearoyl phosphatidylglycerol sodium salt 84 mg; hydrogenated soy phosphatidylcholine 213 mg, together with disodium succinate hexahydrate 27 mg; and sucrose 900 mg. AmBisome may also contain hydrochloric acid and/or sodium hydroxide as pH adjusters. Following reconstitution with Sterile Water for Injection, USP, the resulting pH of the suspension is between 5-6.

AmBisome is a true single bilayer liposomal drug delivery system. Liposomes are closed, spherical vesicles created by mixing specific proportions of amphophilic substances such as phospholipids and cholesterol so that they arrange themselves into multiple concentric bilayer membranes when hydrated in aqueous solutions. Single bilayer liposomes are then formed by microemulsification of multilamellar vesicles using a homogenizer. AmBisome consists of these unilamellar bilayer liposomes with amphotericin B intercalated within the membrane. Due to the nature and quantity of amphophilic substances used, and the lipophilic moiety in the amphotericin B molecule, the drug is an integral part of the overall structure of the AmBisome liposomes. AmBisome contains true liposomes that are less than 100 nm in diameter. A schematic depiction of the liposome is presented below.

Note: Liposomal encapsulation or incorporation into a lipid complex can substantially affect a drug’s functional properties relative to those of the unencapsulated drug or non-lipid associated drug. In addition, different liposomal or lipid-complex products with a common active ingredient may vary from one another in the chemical composition and physical form of the lipid component. Such differences may affect the functional properties of these drug products.

Amphotericin B is a macrocyclic, polyene, antifungal antibiotic produced from a strain of Streptomyces nodosus. Amphotericin B is designated chemically as:

[1R-(1R*,3S*,5R*,6R*,9R*,11R*,15S*,16R*,17R*,18S*,19E,21E,23E,25E,27E,29E,31E,33R*,35S*,36R*,37S*)]-33-[(3-Amino-3,6-dideoxy-β-D-mannopyranosyl)oxy]-1,3,5,6,9,11,17,37-octahydroxy-15,16,18-trimethyl-13-oxo-14,39-dioxabicyclo[33.3.1]nonatriaconta-19,21,23,25,27,29,31-heptaene-36-carboxylic acid (CAS No. 1397-89-3).

Amphotericin B has a molecular formula of C47H73NO17 and a molecular weight of 924.09.

The structure of amphotericin B is shown below:

MICROBIOLOGY

Mechanism of Action

Amphotericin B, the active ingredient of AmBisome, acts by binding to the sterol component, ergosterol, of the cell membrane of susceptible fungi. It forms transmembrane channels leading to alterations in cell permeability through which monovalent ions (NA+, K+, H+, and Cl-) leak out of the cell resulting in cell death. While amphotericin B has a higher affinity for the ergosterol component of the fungal cell membrane, it can also bind to the cholesterol component of the mammalian cell leading to cytotoxicity. AmBisome, the liposomal preparation of amphotericin B, has been shown to penetrate the cell wall of both extracellular and intracellular forms of susceptible fungi.

Resistance

Mutants with decreased susceptibility to amphotericin B have been isolated from several fungal species after serial passage in culture media containing the drug, and from some patients receiving prolonged therapy. Drug combination studies in vitro and in vivo suggest that imidazoles may induce resistance to amphotericin B; however, the clinical relevance of drug resistance has not been established.

Antimicrobial Activity

AmBisome has shown in vitro activity comparable to amphotericin B against the following organisms: Aspergillus fumigatus, Aspergillus flavus, Candida albicans, Candida krusei, Candida lusitaniae, Candida parapsilosis, Candida tropicalis, Cryptococcus neoformans, and Blastomyces dermatitidis.

Susceptibility Testing

For specific information regarding susceptibility test interpretive criteria and associated test methods and quality control standards recognized by FDA for this drug, please see: https://www.fda.gov/STIC.

CLINICAL PHARMACOLOGY

Pharmacokinetics

The assay used to measure amphotericin B in the serum after administration of AmBisome does not distinguish amphotericin B that is complexed with the phospholipids of AmBisome from amphotericin B that is uncomplexed. The pharmacokinetic profile of amphotericin B after administration of AmBisome is based upon total serum concentrations of amphotericin B. The pharmacokinetic profile of amphotericin B was determined in febrile neutropenic cancer and bone marrow transplant patients who received 1-2 hour infusions of 1 to 5 mg/kg/day AmBisome for 3 to 20 days.

The pharmacokinetics of amphotericin B after administration of AmBisome is nonlinear such that there is a greater than proportional increase in serum concentrations with an increase in dose from 1 to 5 mg/kg/day. The pharmacokinetic parameters of total amphotericin B (mean ± SD) after the first dose and at steady state are shown in the table below.

Pharmacokinetic Parameters of AmBisome
Dose | 1 mg/kg/day |  | 2.5 mg/kg/day |  | 5 mg/kg/day
Day | 1 n = 8 | Last n = 7 | 1 n = 7 | Last n = 7 | 1 n = 12 | Last n = 9
Parameters
Cmax (mcg/mL) | 7.3 ± 3.8 | 12.2 ± 4.9 | 17.2 ± 7.1 | 31.4 ± 17.8 | 57.6 ± 21 | 83 ± 35.2
AUC0-24 (mcg•hr/mL) | 27 ± 14 | 60 ± 20 | 65 ± 33 | 197 ± 183 | 269 ± 96 | 555 ± 311
t½ (hr) | 10.7 ± 6.4 | 7 ± 2.1 | 8.1 ± 2.3 | 6.3 ± 2 | 6.4 ± 2.1 | 6.8 ± 2.1
Vss (L/kg) | 0.44 ± 0.27 | 0.14 ± 0.05 | 0.40 ± 0.37 | 0.16 ± 0.09 | 0.16 ± 0.10 | 0.10 ± 0.07
Cl (mL/hr/kg) | 39 ± 22 | 17 ± 6 | 51 ± 44 | 22 ± 15 | 21 ± 14 | 11 ± 6

Distribution

Based on total amphotericin B concentrations measured within a dosing interval (24 hours) after administration of AmBisome, the mean half-life was 7-10 hours. However, based on total amphotericin B concentration measured up to 49 days after dosing of AmBisome, the mean half-life was 100-153 hours. The long terminal elimination half-life is probably a slow redistribution from tissues. Steady state concentrations were generally achieved within 4 days of dosing.

Although variable, mean trough concentrations of amphotericin B remained relatively constant with repeated administration of the same dose over the range of 1 to 5 mg/kg/day, indicating no significant drug accumulation in the serum.

Metabolism

The metabolic pathways of amphotericin B after administration of AmBisome are not known.

Excretion

The mean clearance at steady state was independent of dose. The excretion of amphotericin B after administration of AmBisome has not been studied.

Pharmacokinetics in Special Populations

Renal Impairment

The effect of renal impairment on the disposition of amphotericin B after administration of AmBisome has not been studied. However, AmBisome has been successfully administered to patients with pre-existing renal impairment (see DESCRIPTION OF CLINICAL STUDIES).

Hepatic Impairment

The effect of hepatic impairment on the disposition of amphotericin B after administration of AmBisome is not known.

Pediatric and Elderly Patients

The pharmacokinetics of amphotericin B after administration of AmBisome in pediatric and elderly patients has not been studied; however, AmBisome has been used in pediatric and elderly patients (see DESCRIPTION OF CLINICAL STUDIES).

Gender and Ethnicity

The effect of gender or ethnicity on the pharmacokinetics of amphotericin B after administration of AmBisome is not known.

INDICATIONS AND USAGE

AmBisome is indicated for the following:

- Empirical therapy for presumed fungal infection in febrile, neutropenic patients.
- Treatment of Cryptococcal Meningitis in HIV-infected patients (see DESCRIPTION OF CLINICAL STUDIES).
- Treatment of patients with Aspergillus species, Candida species and/or Cryptococcus species infections (see above for the treatment of Cryptococcal Meningitis) refractory to amphotericin B deoxycholate, or in patients where renal impairment or unacceptable toxicity precludes the use of amphotericin B deoxycholate.
- Treatment of visceral leishmaniasis. In immunocompromised patients with visceral leishmaniasis treated with AmBisome, relapse rates were high following initial clearance of parasites (see DESCRIPTION OF CLINICAL STUDIES).

See DOSAGE AND ADMINISTRATION for recommended doses by indication.

DESCRIPTION OF CLINICAL STUDIES

Eleven clinical studies supporting the efficacy and safety of AmBisome were conducted. This clinical program included both controlled and uncontrolled studies. These studies, which involved 2,171 patients, included patients with confirmed systemic mycoses, empirical therapy, and visceral leishmaniasis.

Nineteen hundred and forty-six (1946) episodes were evaluable for efficacy, of which 1,280 (302 pediatric and 978 adults) were treated with AmBisome.

Three controlled empirical therapy trials compared the efficacy and safety of AmBisome to amphotericin B. One of these studies was conducted in a pediatric population, one in adults, and a third in patients aged 2 years or more. In addition, a controlled empirical therapy trial comparing the safety of AmBisome to Abelcet® (amphotericin B lipid complex) was conducted in patients aged 2 years or more.

One controlled trial compared the efficacy and safety of AmBisome to amphotericin B in HIV patients with cryptococcal meningitis.

One compassionate use study enrolled patients who had failed amphotericin B deoxycholate therapy or who were unable to receive amphotericin B deoxycholate because of renal insufficiency.

Empirical Therapy in Febrile Neutropenic Patients

Study 94-0-002, a randomized, double-blind, comparative multi-center trial, evaluated the efficacy of AmBisome (1.5-6 mg/kg/day) compared with amphotericin B deoxycholate (0.3-1.2 mg/kg/day) in the empirical treatment of 687 adult and pediatric neutropenic patients who were febrile despite having received at least 96 hours of broad spectrum antibacterial therapy. Therapeutic success required (a) resolution of fever during the neutropenic period, (b) absence of an emergent fungal infection, (c) patient survival for at least 7 days post therapy, (d) no discontinuation of therapy due to toxicity or lack of efficacy, and (e) resolution of any study-entry fungal infection.

The overall therapeutic success rates for AmBisome and the amphotericin B deoxycholate were equivalent. Results are summarized in the following table. Note: The categories presented below are not mutually exclusive.

Empirical Therapy in Febrile Neutropenic Patients:
Randomized, Double-Blind Study in 687 Patients
 | AmBisome; 3 mg/kg/day | Amphotericin B; 0.6 mg/kg/day
Number of patients receiving at least one dose of study drug | 343 | 344
Overall Success | 171 (49.9%) | 169 (49.1%)
Fever resolution during neutropenic period | 199 (58%) | 200 (58.1%)
No treatment-emergent fungal infection | 300 (87.5%) | 301 (87.7%)
Survival through 7 days post study drug | 318 (92.7%) | 308 (89.5%)
Study drug not prematurely discontinued due to toxicity or lack of efficacy* | 294 (85.7%) | 280 (81.4%)

* 8 and 10 patients, respectively, were treated as failures due to premature discontinuation alone.

This therapeutic equivalence had no apparent relationship to the use of prestudy antifungal prophylaxis or concomitant granulocytic colony-stimulating factors.

The incidence of mycologically-confirmed, and clinically-diagnosed, emergent fungal infections are presented in the following table. AmBisome and amphotericin B were found to be equivalent with respect to the total number of emergent fungal infections.

Empirical Therapy in Febrile Neutropenic Patients:
Emergent Fungal Infections
 | AmBisome; 3 mg/kg/day | Amphotericin B; 0.6 mg/kg/day
Number of patients receiving at least one dose of study drug | 343 | 344
Mycologically-confirmed fungal infection | 11 (3.2%) | 27 (7.8%)
Clinically-diagnosed fungal infection | 32 (9.3%) | 16 (4.7%)
Total emergent fungal infections | 43 (12.5%) | 43 (12.5%)

Mycologically-confirmed fungal infections at study entry were cured in 8 of 11 patients in the AmBisome group and 7 of 10 in the amphotericin B group.

Study 97-0-034, a randomized, double-blind, comparative multi-center trial, evaluated the safety of AmBisome (3 and 5 mg/kg/day) compared with amphotericin B lipid complex (5 mg/kg/day) in the empirical treatment of 202 adult and 42 pediatric neutropenic patients. One hundred and sixty-six (166) patients received AmBisome (85 patients received 3 mg/kg/day and 81 received 5 mg/kg/day) and 78 patients received amphotericin B lipid complex. The study patients were febrile despite having received at least 72 hours of broad spectrum antibacterial therapy. The primary endpoint of this study was safety. The study was not designed to draw statistically meaningful conclusions related to comparative efficacy and, in fact, Abelcet is not labeled for this indication.

Two supportive, prospective, randomized, open-label, comparative multi-center studies examined the efficacy of two dosages of AmBisome (1 and 3 mg/kg/day) compared to amphotericin B deoxycholate (1 mg/kg/day) in the treatment of neutropenic patients with presumed fungal infections. These patients were undergoing chemotherapy as part of a bone marrow transplant or had hematological disease. Study 104-10 enrolled adult patients (n = 134). Study 104-14 enrolled pediatric patients (n = 214). Both studies support the efficacy equivalence of AmBisome and amphotericin B as empirical therapy in febrile neutropenic patients.

Treatment of Cryptococcal Meningitis in HIV-Infected Patients

Study 94-0-013, a randomized, double-blind, comparative multi-center trial, evaluated the efficacy of AmBisome at doses (3 and 6 mg/kg/day) compared with amphotericin B deoxycholate (0.7 mg/kg/day) for the treatment of cryptococcal meningitis in 266 adult and one pediatric HIV-positive patients (the pediatric patient received amphotericin B deoxycholate). Of the 267 treated patients, 86 received AmBisome 3 mg/kg/day, 94 received 6 mg/kg/day and 87 received amphotericin B deoxycholate; cryptococcal meningitis was documented by a positive CSF culture at baseline in 73, 85 and 76 patients, respectively. Patients received study drug once daily for an induction period of 11 to 21 days. Following induction, all patients were switched to oral fluconazole at 400 mg/day for adults and 200 mg/day for patients less than 13 years of age to complete 10 weeks of protocol-directed therapy. For mycologically evaluable patients, defined as all randomized patients who received at least one dose of study drug, had a positive baseline CSF culture, and had at least one follow-up culture, success was evaluated at week 2 (i.e., 14 ± 4 days), and was defined as CSF culture conversion. Success rates at 2 weeks for AmBisome and amphotericin B deoxycholate are summarized in the following table:

Success Rates at 2 Weeks (CSF Culture Conversion) Study 94-0-013
 | AmBisome; 3 mg/kg/day | AmBisome; 6 mg/kg/day | Amphotericin B; 0.7 mg/kg/day
Success at Week 2 | 35/60 (58.3%); 97.5% CI* = -9.4%, +31% | 36/75 (48%); 97.5% CI* = -18.8%, +19.8% | 29/61 (47.5%)

* 97.5% Confidence Interval for the difference between AmBisome and amphotericin B success rates. A negative value is in favor of amphotericin B. A positive value is in favor of AmBisome.

Success at 10 weeks was defined as clinical success at week 10 plus CSF culture conversion at or prior to week 10. Success rates at 10 weeks in patients with positive baseline culture for cryptococcus species are summarized in the following table and show that the efficacy of AmBisome 6 mg/kg/day approximates the efficacy of the amphotericin B deoxycholate regimen. These data do not support the conclusion that AmBisome 3 mg/kg/day is comparable in efficacy to amphotericin B deoxycholate. The table also presents 10-week survival rates for patients treated in this study.

Success Rates and Survival Rates at Week 10, Study 94-0-013 (see text for definitions)
 | AmBisome; 3 mg/kg/day | AmBisome; 6 mg/kg/day | Amphotericin B; 0.7 mg/kg/day
Success in patients with documented cryptococcal meningitis | 27/73 (37%); 97.5% CI* = -33.7%, +2.4% | 42/85 (49%); 97.5% CI* = -20.9%, +14.5% | 40/76 (53%)
Survival rates | 74/86 (86%); 97.5% CI* = -13.8%, +8.9% | 85/94 (90%); 97.5% CI* = -8.3%, +12.2% | 77/87 (89%)

* 97.5% Confidence Interval for the difference between AmBisome and amphotericin B rates. A negative value is in favor of amphotericin B. A positive value is in favor of AmBisome.

The incidence of infusion-related, cardiovascular and renal adverse events was lower in patients receiving AmBisome compared to amphotericin B deoxycholate (see ADVERSE REACTIONS section for details); therefore, the risks and benefits (advantages and disadvantages) of the different amphotericin B formulations should be taken into consideration when selecting a patient treatment regimen.

Treatment of Patients with Aspergillus Species, Candida Species and/or Cryptococcus Species Infections Refractory to Amphotericin B Deoxycholate, or in Patients Where Renal Impairment or Unacceptable Toxicity Precludes the Use of Amphotericin B Deoxycholate

AmBisome was evaluated in a compassionate use study in hospitalized patients with systemic fungal infections. These patients either had fungal infections refractory to amphotericin B deoxycholate, were intolerant to the use of amphotericin B deoxycholate, or had pre-existing renal insufficiency. Patient recruitment involved 140 infectious episodes in 133 patients, with 53 episodes evaluable for mycological response and 91 episodes evaluable for clinical outcome. Clinical success and mycological eradication occurred in some patients with documented aspergillosis, candidiasis, and cryptococcosis.

Treatment of Visceral Leishmaniasis

AmBisome was studied in patients with visceral leishmaniasis who were infected in the Mediterranean basin with documented or presumed Leishmania infantum. Clinical studies have not provided conclusive data regarding efficacy against L. donovani or L. chagasi.

AmBisome achieved high rates of acute parasite clearance in immunocompetent patients when total doses of 12-30 mg/kg were administered. Most of these immunocompetent patients remained relapse-free during follow-up periods of 6 months or longer. While acute parasite clearance was achieved in most of the immunocompromised patients who received total doses of 30-40 mg/kg, the majority of these patients were observed to relapse in the 6 months following the completion of therapy. Of the 21 immunocompromised patients studied, 17 were coinfected with HIV; approximately half of the HIV-infected patients had AIDS. The following table presents a comparison of efficacy rates among immunocompetent and immunocompromised patients infected in the Mediterranean basin who had no prior treatment or remote prior treatment for visceral leishmaniasis. Efficacy is expressed as both acute parasite clearance at the end of therapy (EOT) and as overall success (clearance with no relapse) during the follow-up period (F/U) of greater than 6 months for immunocompetent and immunocompromised patients:

AmBisome Efficacy in Visceral Leishmaniasis
Immunocompetent Patients
No. of Patients | Parasite (%) Clearance at EOT |  | Overall Success (%); at F/U
87 | 86/87 (98.9) |  | 83/86 (96.5)
Immunocompromised Patients
Regimen | Total Dose | Parasite (%) Clearance at EOT | Overall Success (%); at F/U
100 mg/day X 21 days | 29-38.9 mg/kg | 10/10 (100) | 2/10 (20)
4 mg/kg/day, days 1-5, and 10, 17, 24, 31, 38 | 40 mg/kg | 8/9 (88.9) | 0/7 (0)
TOTAL |  | 18/19 (94.7) | 2/17 (11.8)

When followed for 6 months or more after treatment, the overall success rate among immunocompetent patients was 96.5% and the overall success rate among immunocompromised patients was 11.8% due to relapse in the majority of patients. While case reports have suggested there may be a role for long-term therapy to prevent relapses in HIV coinfected patients (Lopez-Dupla, et al. J Antimicrob Chemother 1993; 32: 657-659), there are no data to date documenting the efficacy or safety of repeat courses of AmBisome or of maintenance therapy with this drug among immunocompromised patients.

CONTRAINDICATIONS

AmBisome is contraindicated in those patients who have demonstrated or have a known hypersensitivity to amphotericin B deoxycholate or any other constituents of the product unless, in the opinion of the treating physician, the benefit of therapy outweighs the risk.

WARNINGS

Anaphylaxis has been reported with amphotericin B deoxycholate and other amphotericin B-containing drugs, including AmBisome. If a severe anaphylactic reaction occurs, the infusion should be immediately discontinued and the patient should not receive further infusions of AmBisome.

PRECAUTIONS

General

As with any amphotericin B-containing product the drug should be administered by medically trained personnel. During the initial dosing period, patients should be under close clinical observation. AmBisome has been shown to be significantly less toxic than amphotericin B deoxycholate; however, adverse events may still occur.

Laboratory Tests

Patient management should include laboratory evaluation of renal, hepatic and hematopoietic function, and serum electrolytes (particularly magnesium and potassium).

Drug-Laboratory Interactions: Serum phosphate false elevation

False elevations of serum phosphate may occur when samples from patients receiving AmBisome are analyzed using the PHOSm assay (e.g. used in Beckman Coulter analyzers including the Synchron LX20). This assay is intended for the quantitative determination of inorganic phosphorus in human serum, plasma or urine samples.

Drug Interactions

No formal clinical studies of drug interactions have been conducted with AmBisome; however, the following drugs are known to interact with amphotericin B and may interact with AmBisome:

Antineoplastic Agents

Concurrent use of antineoplastic agents may enhance the potential for renal toxicity, bronchospasm, and hypotension. Antineoplastic agents should be given concomitantly with caution.

Corticosteroids and Corticotropin (ACTH)

Concurrent use of corticosteroids and ACTH may potentiate hypokalemia, which could predispose the patient to cardiac dysfunction. If used concomitantly, serum electrolytes and cardiac function should be closely monitored.

Digitalis Glycosides

Concurrent use may induce hypokalemia and may potentiate digitalis toxicity. When administered concomitantly, serum potassium levels should be closely monitored.

Flucytosine

Concurrent use of flucytosine may increase the toxicity of flucytosine by possibly increasing its cellular uptake and/or impairing its renal excretion.

Azoles (e.g., ketoconazole, miconazole, clotrimazole, fluconazole, etc.)

In vitro and in vivo animal studies of the combination of amphotericin B and imidazoles suggest that imidazoles may induce fungal resistance to amphotericin B. Combination therapy should be administered with caution, especially in immunocompromised patients.

Leukocyte Transfusions

Acute pulmonary toxicity has been reported in patients simultaneously receiving intravenous amphotericin B and leukocyte transfusions.

Other Nephrotoxic Medications

Concurrent use of amphotericin B and other nephrotoxic medications may enhance the potential for drug-induced renal toxicity. Intensive monitoring of renal function is recommended in patients requiring any combination of nephrotoxic medications.

Skeletal Muscle Relaxants

Amphotericin B-induced hypokalemia may enhance the curariform effect of skeletal muscle relaxants (e.g. tubocurarine) due to hypokalemia. When administered concomitantly, serum potassium levels should be closely monitored.

Carcinogenesis, Mutagenesis, Impairment of Fertility

No long-term studies in animals have been performed to evaluate carcinogenic potential of AmBisome. AmBisome has not been tested to determine its mutagenic potential. A Segment I Reproductive Study in rats found an abnormal estrous cycle (prolonged diestrus) and decreased number of corpora lutea in the high-dose groups (10 and 15 mg/kg, doses equivalent to human doses of 1.6 and 2.4 mg/kg based on body surface area considerations). AmBisome did not affect fertility or days to copulation. There were no effects on male reproductive function.

Pregnancy

There have been no adequate and well-controlled studies of AmBisome in pregnant women. Systemic fungal infections have been successfully treated in pregnant women with amphotericin B deoxycholate, but the number of cases reported has been small.

Segment II studies in both rats and rabbits have concluded that AmBisome had no teratogenic potential in these species. In rats, the maternal non-toxic dose of AmBisome was estimated to be 5 mg/kg (equivalent to 0.16 to 0.8 times the recommended human clinical dose range of 1 to 5 mg/kg) and in rabbits, 3 mg/kg (equivalent to 0.2 to 1 times the recommended human clinical dose range), based on body surface area correction. Rabbits receiving the higher doses, (equivalent to 0.5 to 2 times the recommended human dose) of AmBisome experienced a higher rate of spontaneous abortions than did the control groups. AmBisome should only be used during pregnancy if the possible benefits to be derived outweigh the potential risks involved.

Nursing Mothers

Many drugs are excreted in human milk; however, it is not known whether AmBisome is excreted in human milk. Due to the potential for serious adverse reactions in breastfed infants, a decision should be made whether to discontinue nursing or whether to discontinue the drug, taking into account the importance of the drug to the mother.

Pediatric Use

Pediatric patients, age 1 month to 16 years, with presumed fungal infection (empirical therapy), confirmed systemic fungal infections or with visceral leishmaniasis have been successfully treated with AmBisome. In studies which included 302 pediatric patients administered AmBisome, there was no evidence of any differences in efficacy or safety of AmBisome compared to adults. Since pediatric patients have received AmBisome at doses comparable to those used in adults on a per kilogram body weight basis, no dosage adjustment is required in this population. Safety and effectiveness in pediatric patients below the age of one month have not been established (See DESCRIPTION OF CLINICAL STUDIES - Empirical Therapy in Febrile Neutropenic Patients and DOSAGE AND ADMINISTRATION).

Elderly Patients

Experience with AmBisome in the elderly (65 years or older) comprised 72 patients. It has not been necessary to alter the dose of AmBisome for this population. As with most other drugs, elderly patients receiving AmBisome should be carefully monitored.

ADVERSE REACTIONS

The following adverse events are based on the experience of 592 adult patients (295 treated with AmBisome and 297 treated with amphotericin B deoxycholate) and 95 pediatric patients (48 treated with AmBisome and 47 treated with amphotericin B deoxycholate) in Study 94-0-002, a randomized double-blind, multi-center study in febrile, neutropenic patients. AmBisome and amphotericin B were infused over two hours.

The incidence of common adverse events (incidence of 10% or greater) occurring with AmBisome compared to amphotericin B deoxycholate, regardless of relationship to study drug, is shown in the following table:

Empirical Therapy Study 94-0-002

Common Adverse Events

Adverse Event by Body System | AmBisome N = 343 % | Amphotericin B N = 344 %
Body as a Whole
Abdominal pain; Asthenia; Back pain; Blood product transfusion reaction; Chills; Infection; Pain; Sepsis | 19.8; 13.1; 12; 18.4; 47.5; 11.1; 14; 14 | 21.8; 10.8; 7.3; 18.6; 75.9; 9.3; 12.8; 11.3
Cardiovascular System
Chest pain; Hypertension; Hypotension; Tachycardia | 12; 7.9; 14.3; 13.4 | 11.6; 16.3; 21.5; 20.9
Digestive System
Diarrhea; Gastrointestinal hemorrhage; Nausea; Vomiting | 30.3; 9.9; 39.7; 31.8 | 27.3; 11.3; 38.7; 43.9
Metabolic and Nutritional Disorders
Alkaline phosphatase increased; ALT (SGPT) increased; AST (SGOT) increased; Bilirubinemia; BUN increased; Creatinine increased; Edema; Hyperglycemia; Hypernatremia; Hypervolemia; Hypocalcemia; Hypokalemia; Hypomagnesemia; Peripheral edema | 22.2; 14.6; 12.8; 18.1; 21; 22.4; 14.3; 23; 4.1; 12.2; 18.4; 42.9; 20.4; 14.6 | 19.2; 14; 12.8; 19.2; 31.1; 42.2; 14.8; 27.9; 11; 15.4; 20.9; 50.6; 25.6; 17.2
Nervous System
Anxiety; Confusion; Headache; Insomnia | 13.7; 11.4; 19.8; 17.2 | 11; 13.4; 20.9; 14.2
Respiratory System
Cough increased; Dyspnea; Epistaxis; Hypoxia; Lung disorder; Pleural effusion; Rhinitis | 17.8; 23; 14.9; 7.6; 17.8; 12.5; 11.1 | 21.8; 29.1; 20.1; 14.8; 17.4; 9.6; 11
Skin and Appendages
Pruritus; Rash; Sweating | 10.8; 24.8; 7 | 10.2; 24.4; 10.8
Urogenital System
Hematuria | 14 | 14

AmBisome was well tolerated. AmBisome had a lower incidence of chills, hypertension, hypotension, tachycardia, hypoxia, hypokalemia, and various events related to decreased kidney function as compared to amphotericin B deoxycholate.

In pediatric patients (16 years of age or less) in this double-blind study, AmBisome compared to amphotericin B deoxycholate, had a lower incidence of hypokalemia (37% versus 55%), chills (29% versus 68%), vomiting (27% versus 55%), and hypertension (10% versus 21%). Similar trends, although with a somewhat lower incidence, were observed in open-label, randomized Study 104-14 involving 205 febrile neutropenic pediatric patients (141 treated with AmBisome and 64 treated with amphotericin B deoxycholate). Pediatric patients appear to have more tolerance than older individuals for the nephrotoxic effects of amphotericin B deoxycholate.

The following adverse events are based on the experience of 244 patients (202 adult and 42 pediatric patients) of whom 85 patients were treated with AmBisome 3 mg/kg, 81 patients were treated with AmBisome 5 mg/kg and 78 patients were treated with amphotericin B lipid complex 5 mg/kg in Study 97-0-034, a randomized, double-blind, multi-center study in febrile, neutropenic patients. AmBisome and amphotericin B lipid complex were infused over two hours. The incidence of adverse events occurring in more than 10% of subjects in one or more arms, regardless of relationship to study drug, are summarized in the following table:

Empirical Therapy Study 97-0-034

Common Adverse Events

Adverse Event by Body System | AmBisome 3 mg/kg/day N = 85 % | AmBisome 5 mg/kg/day N = 81 % | Amphotericin B Lipid Complex 5 mg/kg/day N = 78 %
Body as a Whole
Abdominal pain; Asthenia; Chills/rigors; Sepsis; Transfusion reaction | 12.9; 8.2; 40; 12.9; 10.6 | 9.9; 6.2; 48.1; 7.4; 8.6 | 11.5; 11.5; 89.7; 11.5; 5.1
Cardiovascular System
Chest pain; Hypertension; Hypotension; Tachycardia | 8.2; 10.6; 10.6; 9.4 | 11.1; 19.8; 7.4; 18.5 | 6.4; 23.1; 19.2; 23.1
Digestive System
Diarrhea; Nausea; Vomiting | 15.3; 25.9; 22.4 | 17.3; 29.6; 25.9 | 14.1; 37.2; 30.8
Metabolic and Nutritional Disorders
Alkaline phosphatase increased; Bilirubinemia; BUN increased; Creatinine increased; Edema; Hyperglycemia; Hypervolemia; Hypocalcemia; Hypokalemia; Hypomagnesemia; Liver function tests abnormal | 7.1; 16.5; 20; 20; 12.9; 8.2; 8.2; 10.6; 37.6; 15.3; 10.6 | 8.6; 11.1; 18.5; 18.5; 12.3; 8.6; 11.1; 4.9; 43.2; 25.9; 7.4 | 12.8; 11.5; 28.2; 48.7; 12.8; 14.1; 14.1; 5.1; 39.7; 15.4; 11.5
Nervous System
Anxiety; Confusion; Headache | 10.6; 12.9; 9.4 | 7.4; 8.6; 17.3 | 9; 3.8; 10.3
Respiratory System
Dyspnea; Epistaxis; Hypoxia; Lung disorder | 17.6; 10.6; 7.1; 14.1 | 22.2; 8.6; 6.2; 13.6 | 23.1; 14.1; 20.5; 15.4
Skin and Appendages
Rash | 23.5 | 22.2 | 14.1

The following adverse events are based on the experience of 267 patients (266 adult patients and 1 pediatric patient) of whom 86 patients were treated with AmBisome 3 mg/kg, 94 patients were treated with AmBisome 6 mg/kg and 87 patients were treated with amphotericin B deoxycholate 0.7 mg/kg in Study 94-0-013 a randomized, double-blind, comparative multi-center trial, in the treatment of cryptococcal meningitis in HIV-positive patients. The incidence of adverse events occurring in more than 10% of subjects in one or more arms regardless of relationship to study drug are summarized in the following table:

Cryptococcal Meningitis Therapy Study 94-0-013

Common Adverse Events

Adverse Event by Body System | AmBisome 3 mg/kg/day N = 86 % | AmBisome 6 mg/kg/day N = 94 % | Amphotericin B 0.7 mg/kg/day N = 87 %
Body as a Whole
Abdominal pain; Infection; Procedural Complication | 7; 12.8; 8.1 | 7.4; 11.7; 9.6 | 10.3; 6.9; 10.3
Cardiovascular System
Phlebitis | 9.3 | 10.6 | 25.3
Digestive System
Anorexia; Constipation; Diarrhea; Nausea; Vomiting | 14; 15.1; 10.5; 16.3; 10.5 | 9.6; 14.9; 16; 21.3; 21.3 | 11.5; 20.7; 10.3; 25.3; 20.7
Hemic and Lymphatic System
Anemia; Leukopenia; Thrombocytopenia | 26.7; 15.1; 5.8 | 47.9; 17; 12.8 | 43.7; 17.2; 6.9
Metabolic and Nutritional Disorders
Bilirubinemia; BUN increased; Creatinine increased; Hyperglycemia; Hypocalcemia; Hypokalemia; Hypomagnesemia; Hyponatremia; Liver Function Tests Abnormal | 0; 9.3; 18.6; 9.3; 12.8; 31.4; 29.1; 11.6; 12.8 | 8.5; 7.4; 39.4; 12.8; 17; 51.1; 48.9; 8.5; 4.3 | 12.6; 10.3; 43.7; 17.2; 13.8; 48.3; 40.2; 9.2; 9.2
Nervous System
Dizziness; Insomnia | 7; 22.1 | 8.5; 17 | 10.3; 20.7
Respiratory System
Cough Increased | 8.1 | 2.1 | 10.3
Skin and Appendages
Rash | 4.7 | 11.7 | 4.6

Infusion-Related Reactions

In Study 94-0-002, the large, double-blind study of pediatric and adult febrile neutropenic patients, no premedication to prevent infusion-related reaction was administered prior to the first dose of study drug (Day 1). AmBisome-treated patients had a lower incidence of infusion-related fever (17% versus 44%), chills/rigors (18% versus 54%) and vomiting (6% versus 8%) on Day 1 as compared to amphotericin B deoxycholate-treated patients.

The incidence of infusion-related reactions on Day 1 in pediatric and adult patients is summarized in the following table:

Incidence of Day 1 Infusion-Related Reactions (IRR) By Patient Age
 | Pediatric Patients (≤ 16 years of age) |  | Adult Patients (> 16 years of age)
 | AmBisome 3 mg/kg/day | Amphotericin B 0.6 mg/kg/day | AmBisome 3 mg/kg/day | Amphotericin B 0.6 mg/kg/day
Total number of patients receiving at least one dose of study drug | 48 | 47 | 295 | 297
Patients with fever* increase ≥ 1.0oC | 6 (13%) | 22 (47%) | 52 (18%) | 128 (43%)
Patients with chills/rigors | 4 (8%) | 22 (47%) | 59 (20%) | 165 (56%)
Patients with nausea | 4 (8%) | 4 (9%) | 38 (13%) | 31 (10%)
Patients with vomiting | 2 (4%) | 7 (15%) | 19 (6%) | 21 (7%)
Patients with other reactions | 10 (21%) | 13 (28%) | 47 (16%) | 69 (23%)

* Day 1 body temperature increased above the temperature taken within 1 hour prior to infusion (preinfusion temperature) or above the lowest infusion value (no preinfusion temperature recorded).

Cardiorespiratory events, except for vasodilatation (flushing), during all study drug infusions were more frequent in amphotericin B-treated patients as summarized in the following table:

Incidence of Infusion-Related Cardiorespiratory Events
Event | AmBisome; 3 mg/kg/day; N = 343 | Amphotericin B; 0.6 mg/kg/day; N = 344
Hypotension | 12 (3.5%) | 28 (8.1%)
Tachycardia | 8 (2.3%) | 43 (12.5%)
Hypertension | 8 (2.3%) | 39 (11.3%)
Vasodilatation | 18 (5.2%) | 2 (0.6%)
Dyspnea | 16 (4.7%) | 25 (7.3%)
Hyperventilation | 4 (1.2%) | 17 (4.9%)
Hypoxia | 1 (0.3%) | 22 (6.4%)

The percentage of patients who received drugs either for the treatment or prevention of infusion-related reactions (e.g., acetaminophen, diphenhydramine, meperidine and hydrocortisone) was lower in AmBisome-treated patients compared with amphotericin B deoxycholate-treated patients.

In the empirical therapy study 97-0-034, on Day 1, where no premedication was administered, the overall incidence of infusion-related events of chills/rigors was significantly lower for patients administered AmBisome compared with amphotericin B lipid complex. Fever, chills/rigors and hypoxia were significantly lower for each AmBisome group compared with the amphotericin B lipid complex group. The infusion-related event hypoxia was reported for 11.5% of amphotericin B lipid complex-treated patients compared with 0% of patients administered 3 mg/kg per day AmBisome and 1.2% of patients treated with 5 mg/kg per day AmBisome.

Incidence of Day 1 Infusion-Related Reactions (IRR) Chills/Rigors Empirical Therapy Study 97-0-034
 | AmBisome |  |  | Amphotericin B lipid complex; 5 mg/kg/day
 | 3 mg/kg/day | 5 mg/kg/day | BOTH | Amphotericin B lipid complex; 5 mg/kg/day
Total number of patients | 85 | 81 | 166 | 78
Patients with Chills/Rigors (Day 1) | 16 (18.8%) | 19 (23.5%) | 35 (21.1%) | 62 (79.5%)
Patients with other notable reactions:
Fever (>1.0oC increase in temperature) | 20 (23.5%) | 16 (19.8%) | 36 (21.7%) | 45 (57.7%)
Nausea | 9 (10.6%) | 7 (8.6%) | 16 (9.6%) | 9 (11.5%)
Vomiting | 5 (5.9%) | 5 (6.2%) | 10 (6%) | 11 (14.1%)
Hypertension | 4 (4.7%) | 7 (8.6%) | 11 (6.6%) | 12 (15.4%)
Tachycardia | 2 (2.4%) | 8 (9.9%) | 10 (6%) | 14 (17.9%)
Dyspnea | 4 (4.7%) | 8 (9.9%) | 12 (7.2%) | 8 (10.3%)
Hypoxia | 0 | 1 (1.2%) | 1 (< 1%) | 9 (11.5%)

Day 1 body temperature increased above the temperature taken within 1 hour prior to infusion (preinfusion temperature) or above the lowest infusion value (no preinfusion temperature recorded).
Patients were not administered premedications to prevent infusion-related reactions prior to the Day 1 study drug infusion.

In Study 94-0-013, a randomized, double-blind, multicenter trial comparing AmBisome and amphotericin B deoxycholate as initial therapy for cryptococcal meningitis, premedications to prevent infusion-related reactions were permitted. AmBisome-treated patients had a lower incidence of fever, chills/rigors and respiratory adverse events as summarized in the following table:

Incidence of Infusion-Related Reactions Study 94-0-013
 | AmBisome; 3 mg/kg/day | AmBisome; 6 mg/kg/day | Amphotericin B; 0.7 mg/kg/day
Total number of patients receiving at least one dose of study drug | 86 | 94 | 87
Patients with fever increase of >1°C | 6 (7%) | 8 (9%) | 24 (28%)
Patients with chills/rigors | 5 (6%) | 8 (9%) | 42 (48%)
Patients with nausea | 11 (13%) | 13 (14%) | 18 (20%)
Patients with vomiting | 14 (16%) | 13 (14%) | 16 (18%)
Respiratory adverse events | 0 | 1 (1%) | 8 (9%)

There have been a few reports of flushing, back pain with or without chest tightness, and chest pain associated with AmBisome administration; on occasion this has been severe. Where these symptoms were noted, the reaction developed within a few minutes after the start of infusion and disappeared rapidly when the infusion was stopped. The symptoms do not occur with every dose and usually do not recur on subsequent administrations when the infusion rate is slowed.

Toxicity and Discontinuation of Dosing

In Study 94-0-002, a significantly lower incidence of grade 3 or 4 toxicity was observed in the AmBisome group compared with the amphotericin B group. In addition, nearly three times as many patients administered amphotericin B required a reduction in dose due to toxicity or discontinuation of study drug due to an infusion-related reaction compared with those administered AmBisome.

In empirical therapy study 97-0-034, a greater proportion of patients in the amphotericin B lipid complex group discontinued the study drug due to an adverse event than in the AmBisome groups.

Less Common Adverse Events

The following adverse events also have been reported in 2% to 10% of AmBisome-treated patients receiving chemotherapy or bone marrow transplantation, or who had HIV disease in six comparative, clinical trials:

Body as a Whole

Abdomen enlarged, allergic reaction, cellulitis, cell-mediated immunological reaction, face edema, graft-versus-host disease, malaise, neck pain, and procedural complication.

Cardiovascular System

Arrhythmia, atrial fibrillation, bradycardia, cardiac arrest, cardiomegaly, hemorrhage, postural hypotension, valvular heart disease, vascular disorder, and vasodilatation (flushing).

Digestive System

Anorexia, constipation, dry mouth/nose, dyspepsia, dysphagia, eructation, fecal incontinence, flatulence, hemorrhoids, gum/oral hemorrhage, hematemesis, hepatocellular damage, hepatomegaly, liver function test abnormal, ileus, mucositis, rectal disorder, stomatitis, ulcerative stomatitis, and veno-occlusive liver disease.

Hemic & Lymphatic System

Anemia, coagulation disorder, ecchymosis, fluid overload, petechia, prothrombin decreased, prothrombin increased, and thrombocytopenia.

Metabolic & Nutritional Disorders

Acidosis, amylase increased, hyperchloremia, hyperkalemia, hypermagnesemia, hyperphosphatemia, hyponatremia, hypophosphatemia, hypoproteinemia, lactate dehydrogenase increased, nonprotein nitrogen (NPN) increased, and respiratory alkalosis.

Musculoskeletal System

Arthralgia, bone pain, dystonia, myalgia, and rigors.

Nervous System

Agitation, coma, convulsion, cough, depression, dysesthesia, dizziness, hallucinations, nervousness, paresthesia, somnolence, thinking abnormality, and tremor.

Respiratory System

Asthma, atelectasis, hemoptysis, hiccup, hyperventilation, influenza-like symptoms, lung edema, pharyngitis, pneumonia, respiratory insufficiency, respiratory failure, and sinusitis.

Skin & Appendages

Alopecia, dry skin, herpes simplex, injection site inflammation, maculopapular rash, purpura, skin discoloration, skin disorder, skin ulcer, urticaria, and vesiculobullous rash.

Special Senses

Conjunctivitis, dry eyes, and eye hemorrhage.

Urogenital System

Abnormal renal function, acute kidney failure, acute renal failure, dysuria, kidney failure, toxic nephropathy, urinary incontinence, and vaginal hemorrhage.

Post-marketing Experience

The following infrequent adverse experiences have been reported in post-marketing surveillance, in addition to those mentioned above: angioedema, erythema, urticaria, bronchospasm, cyanosis/hypoventilation, pulmonary edema, agranulocytosis, hemorrhagic cystitis, and rhabdomyolysis.

Clinical Laboratory Values

The effect of AmBisome on renal and hepatic function and on serum electrolytes was assessed from laboratory values measured repeatedly in Study 94-0-002. The frequency and magnitude of hepatic test abnormalities were similar in the AmBisome and amphotericin B groups. Nephrotoxicity was defined as creatinine values increasing 100% or more over pretreatment levels in pediatric patients, and creatinine values increasing 100% or more over pretreatment levels in adult patients, provided the peak creatinine concentration was > 1.2 mg/dL. Hypokalemia was defined as potassium levels ≤ 2.5 mmol/L any time during treatment.

Incidence of nephrotoxicity, mean peak serum creatinine concentration, mean change from baseline in serum creatinine, and incidence of hypokalemia in the double-blind, randomized study were lower in the AmBisome group as summarized in the following table:

Study 94-0-002 Laboratory Evidence of Nephrotoxicity
 | AmBisome; 3 mg/kg/day | Amphotericin B; 0.6 mg/kg/day
Total number of patients receiving at least one dose of study drug | 343 | 344
Nephrotoxicity | 64 (18.7%) | 116 (33.7%)
Mean peak creatinine | 1.24 mg/dL | 1.52 mg/dL
Mean change from baseline in creatinine | 0.48 mg/dL | 0.77 mg/dL
Hypokalemia | 23 (6.7%) | 40 (11.6%)

The effect of AmBisome (3 mg/kg/day) vs. amphotericin B (0.6 mg/kg/day) on renal function in adult patients enrolled in this study is illustrated in the following figure:

In empirical therapy study 97-0-034, the incidence of nephrotoxicity as measured by increases of serum creatinine from baseline was significantly lower for patients administered AmBisome (individual dose groups and combined) compared with amphotericin B lipid complex.

Incidence of Nephrotoxicity

Empirical Therapy Study 97-0-034

 | AmBisome |  |  | Amphotericin B lipid complex; 5 mg/kg/day
 | 3 mg/kg/day | 5 mg/kg/day | BOTH | Amphotericin B lipid complex; 5 mg/kg/day
Total number of patients | 85 | 81 | 166 | 78
Number with nephrotoxicity
1.5X baseline serum creatinine value | 25 (29.4%) | 21 (25.9%) | 46 (27.7%) | 49 (62.8%)
2X baseline serum creatinine value | 12 (14.1%) | 12 (14.8%) | 24 (14.5%) | 33 (42.3%)

The following graph shows the average serum creatinine concentrations in the compassionate use study and shows that there is a drop from pretreatment concentrations for all patients, especially those with elevated (greater than 1.7 mg/dL) pretreatment creatinine concentrations.

The incidence of nephrotoxicity in Study 94-0-013 comparative trial in cryptococcal meningitis was lower in the AmBisome groups as shown in the following table:

Laboratory Evidence of Nephrotoxicity Study 94-0-013
 | AmBisome; 3 mg/kg/day | AmBisome; 6 mg/kg/day | Amphotericin B; 0.7 mg/kg/day
Total number of patients receiving at least one dose of study drug | 86 | 94 | 87
Number with Nephrotoxicity (%)
1.5X baseline serum creatinine | 30 (35%) | 44 (47%) | 52 (60%)
2X baseline serum creatinine | 12 (14%) | 20 (21%) | 29 (33%)

OVERDOSAGE

The toxicity of AmBisome due to overdose has not been defined. Repeated daily doses up to 10 mg/kg in pediatric patients and 15 mg/kg in adult patients have been administered in clinical trials with no reported dose-related toxicity.

Management

If overdosage should occur, cease administration immediately. Symptomatic supportive measures should be instituted. Particular attention should be given to monitoring renal function. Hemodialysis or peritoneal dialysis do not appear to significantly affect the elimination of AmBisome.

DOSAGE AND ADMINISTRATION

AmBisome is not interchangeable or substitutable on a mg per mg basis with other amphotericin B products. Different amphotericin B products are not equivalent in terms of pharmacodynamics, pharmacokinetics and dosing.

AmBisome should be administered by intravenous infusion, using a controlled infusion device, over a period of approximately 120 minutes.

An in-line membrane filter may be used for the intravenous infusion of AmBisome, provided THE MEAN PORE DIAMETER OF THE FILTER IS NOT LESS THAN 1.0 MICRON.

NOTE: An existing intravenous line must be flushed with 5% Dextrose Injection prior to infusion of AmBisome. If this is not feasible, AmBisome must be administered through a separate line.

Infusion time may be reduced to approximately 60 minutes in patients in whom the treatment is well-tolerated. If the patient experiences discomfort during infusion, the duration of infusion may be increased.

The recommended initial dose of AmBisome for each indication for adult and pediatric patients is as follows:

Indication | Dose (mg/kg/day)
Empirical therapy | 3
Systemic fungal infections:; Aspergillus Candida Cryptococcus | 3 - 5
Cryptococcal meningitis in HIV-infected patients; (see DESCRIPTION OF CLINICAL STUDIES) | 6

Dosing and rate of infusion should be individualized to the needs of the specific patient to ensure maximum efficacy while minimizing systemic toxicities or adverse events.

Doses recommended for visceral leishmaniasis are presented below:

Visceral Leishmaniasis | Dose (mg/kg/day)
Immunocompetent patients | 3 (days 1 - 5) and; 3 on days 14, 21
Immunocompromised patients | 4 (days 1 - 5) and; 4 on days 10, 17, 24, 31, 38

For immunocompetent patients who do not achieve parasitic clearance with the recommended dose, a repeat course of therapy may be useful.

For immunocompromised patients who do not clear parasites or who experience relapses, expert advice regarding further treatment is recommended. For additional information, see DESCRIPTION OF CLINICAL STUDIES.

Directions for Reconstitution, Filtration and Dilution

Read This Entire Section Carefully Before Beginning Reconstitution

AmBisome must be reconstituted using Sterile Water for Injection, USP (without a bacteriostatic agent). Vials of AmBisome containing 50 mg of amphotericin B are prepared as follows:

Reconstitution

1. Aseptically add 12 mL of Sterile Water for Injection, USP to each AmBisome vial to yield a preparation containing 4 mg amphotericin B/mL.
  CAUTION: DO NOT RECONSTITUTE WITH SALINE OR ADD SALINE TO THE RECONSTITUTED CONCENTRATION, OR MIX WITH OTHER DRUGS. The use of any solution other than those recommended, or the presence of a bacteriostatic agent in the solution, may cause precipitation of AmBisome.
2. Immediately after the addition of water, SHAKE THE VIAL VIGOROUSLY for 30 seconds to completely disperse the AmBisome. AmBisome forms a yellow, translucent suspension. Visually inspect the vial for particulate matter and continue shaking until completely dispersed.

Filtration and Dilution

3. Calculate the amount of reconstituted (4 mg/mL) AmBisome to be further diluted.
4. Withdraw this amount of reconstituted AmBisome into a sterile syringe.
5. Attach the 5 micron filter provided to the syringe. Inject the syringe contents through the filter, into the appropriate amount of 5% Dextrose Injection (use only one filter per vial of AmBisome).
6. AmBisome must be diluted with 5% Dextrose Injection to a final concentration of 1 to 2 mg/mL prior to administration. Lower concentrations (0.2 to 0.5 mg/mL) may be appropriate for infants and small children to provide sufficient volume for infusion. DISCARD PARTIALLY USED VIALS.

STORAGE OF AMBISOME

Unopened vials of lyophilized material are to be stored at temperatures up to 25°C (77°F).

Storage of Reconstituted Product Concentrate

The reconstituted product concentrate may be stored for up to 24 hours at 2°-8°C (36°-46°F) following reconstitution with Sterile Water for Injection, USP. Do not freeze.

Storage of Diluted Product

Injection of AmBisome should commence within 6 hours of dilution with 5% Dextrose Injection.

As with all parenteral drug products, the reconstituted AmBisome should be inspected visually for particulate matter and discoloration prior to administration, whenever solution and container permit. Do not use material if there is any evidence of precipitation or foreign matter. Aseptic technique must be strictly observed in all handling, since no preservative or bacteriostatic agent is present in AmBisome or in the materials specified for reconstitution and dilution.

HOW SUPPLIED

AmBisome for Injection is available as an individual carton (NDC 0469-3051-30).

Each carton contains one pre-packaged, disposable sterile 5 micron filter.

Rx only

Marketed by:
Astellas Pharma US, Inc.
Northbrook, IL 60062

Manufactured by:
Gilead Sciences, Inc.
Foster City, CA 94404

AmBisome® is a registered trademark of Gilead Sciences, Inc.
All other trademarks and registered trademarks are the property of their respective owners.

Revised Month: 11/2024

420840-AMB-USA

Principal Display Panel

AmBisome

(amphotericin B) liposome for injection

equivalent to

50 mg

amphotericin B

For Intravenous Infusion Only

Single-Use Vial